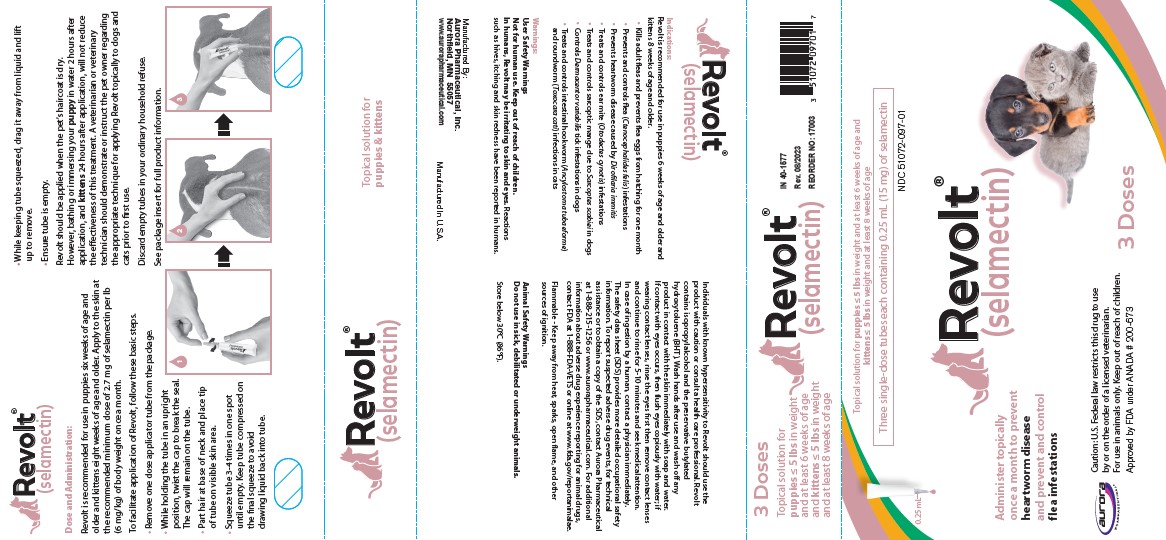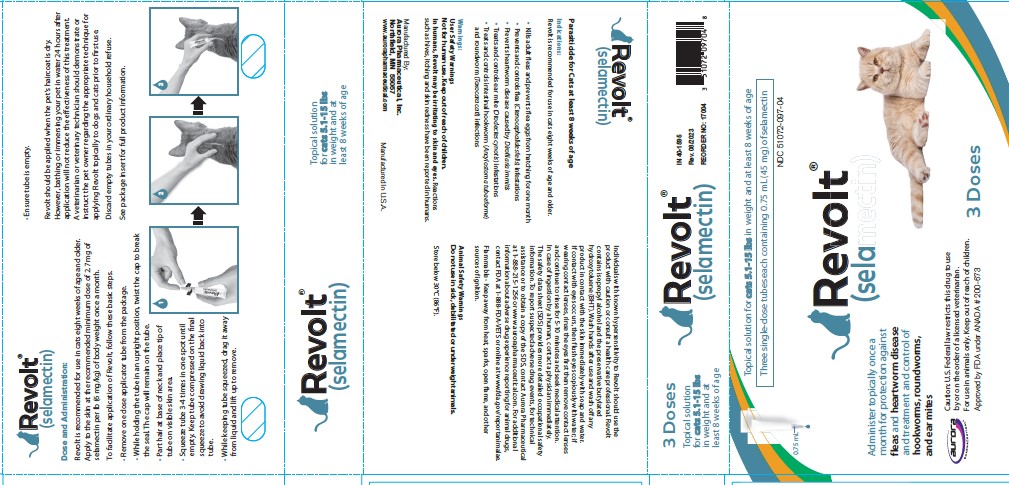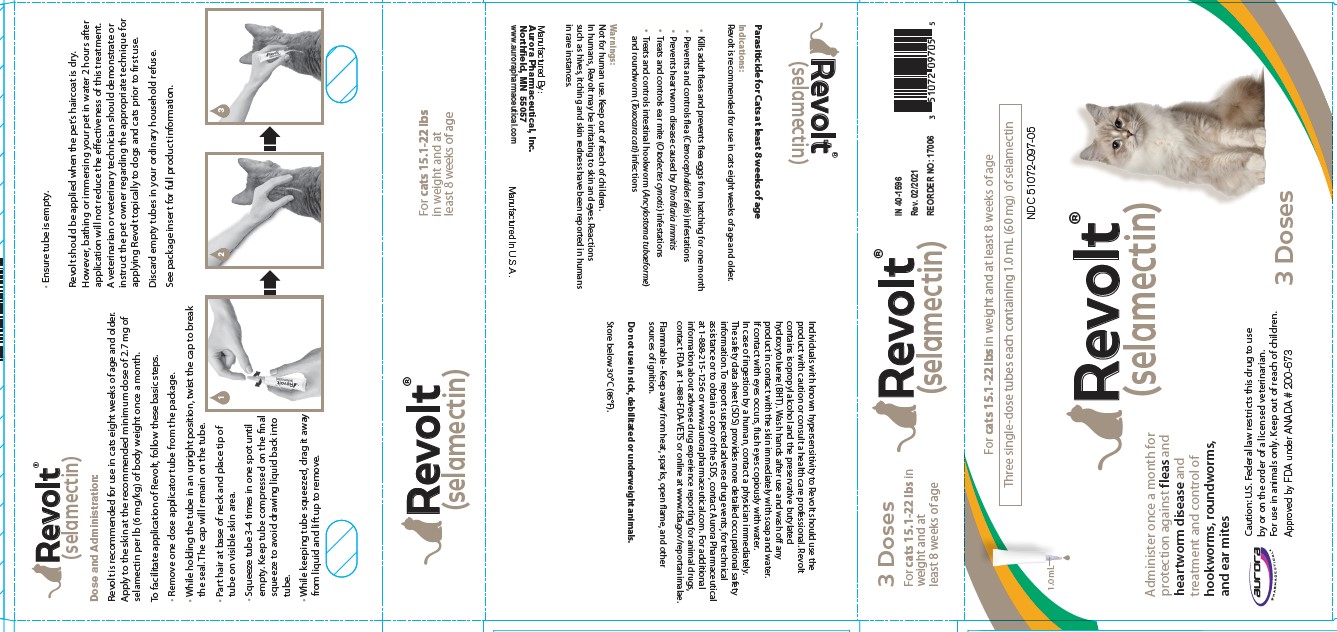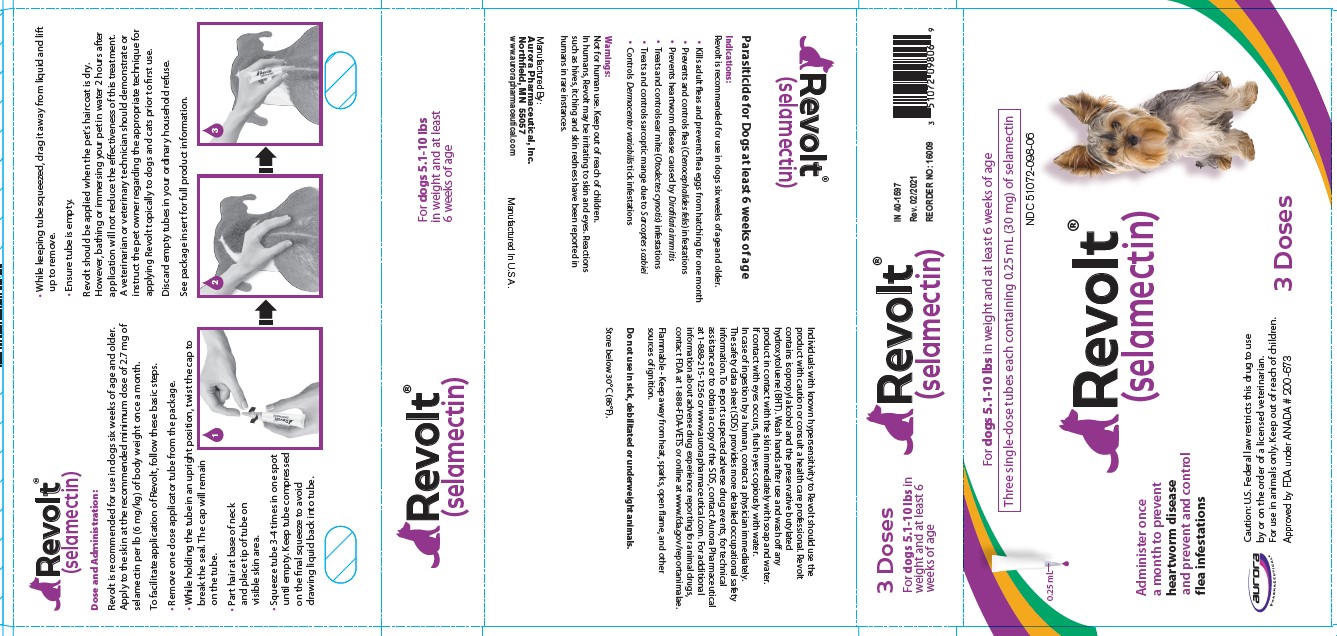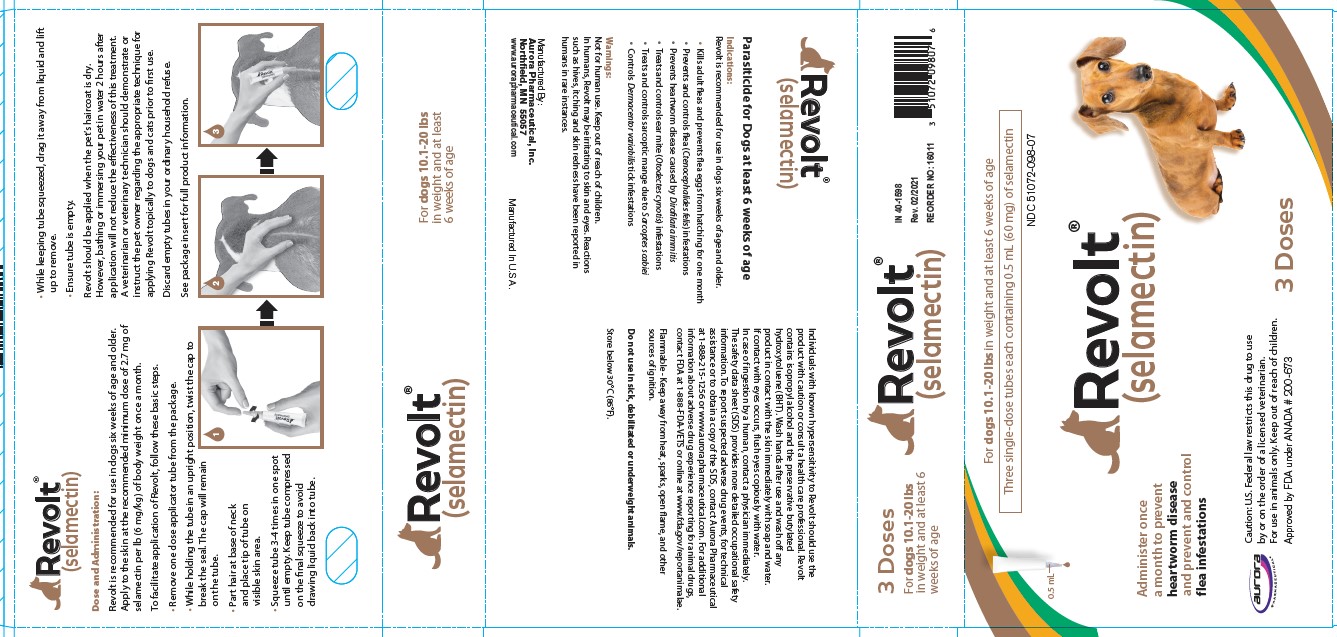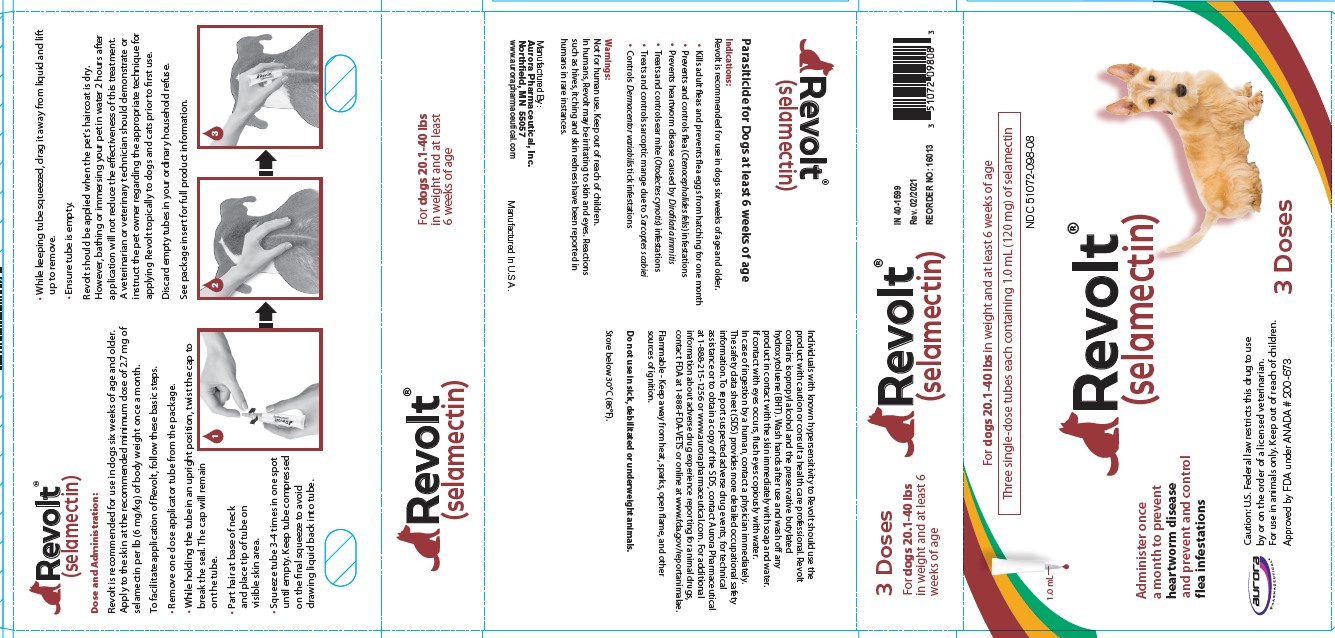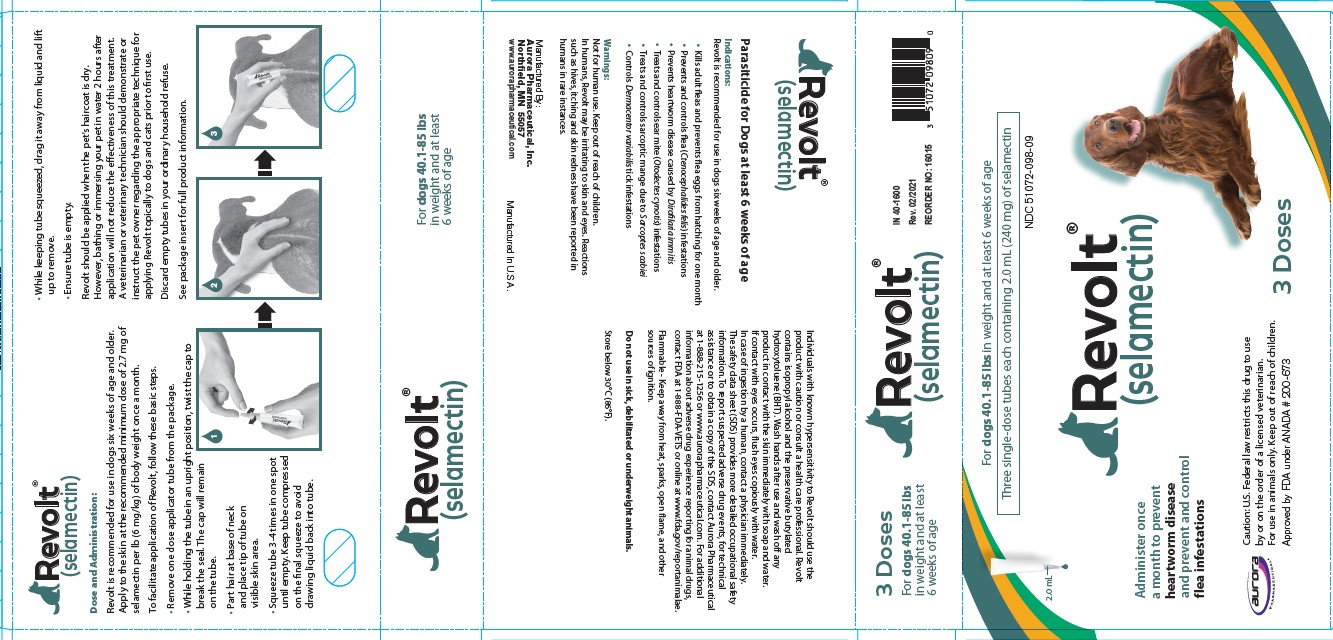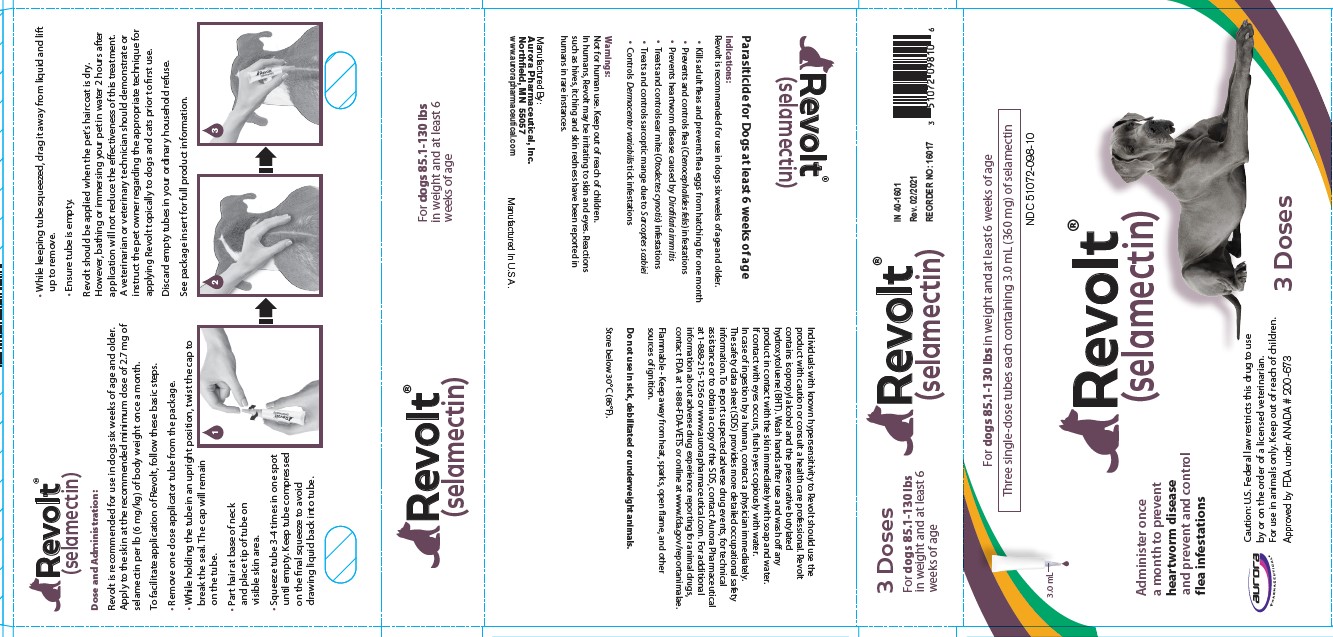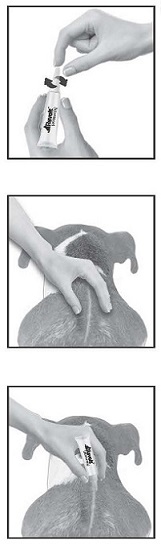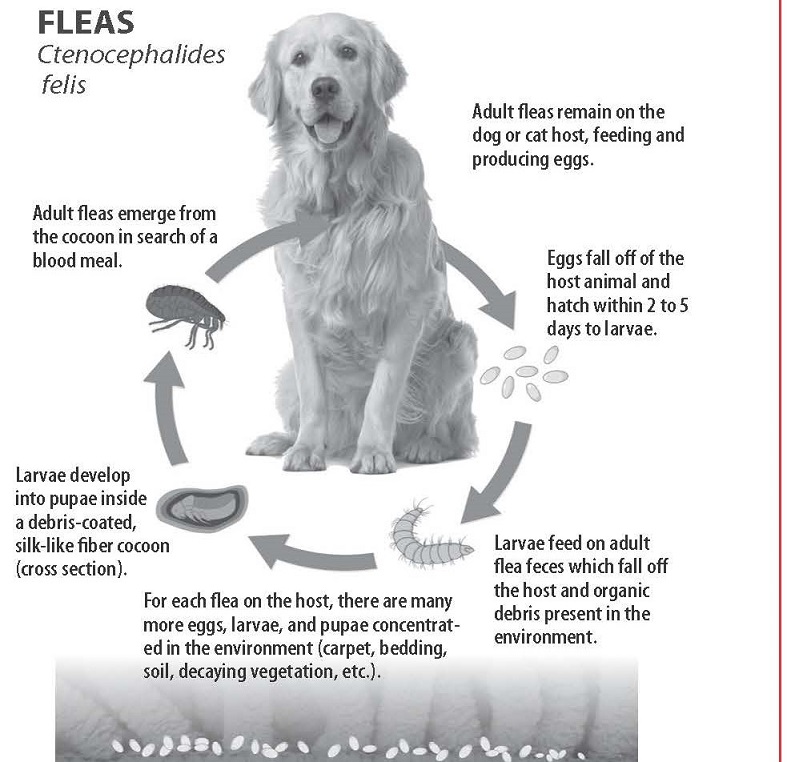 DRUG LABEL: Revolt
NDC: 51072-097 | Form: SOLUTION
Manufacturer: Aurora Pharmaceutical, Inc.
Category: animal | Type: PRESCRIPTION ANIMAL DRUG LABEL
Date: 20250616

ACTIVE INGREDIENTS: SELAMECTIN 60 mg/1 mL
INACTIVE INGREDIENTS: ISOPROPYL ALCOHOL; BUTYLATED HYDROXYTOLUENE

Revolt® (selamectin)
Topical Parasiticide for Dogs and Cats

CAUTION:

US Federal law restricts this drug to use by or on the order of a licensed veterinarian.

DESCRIPTION:

Revolt (selamectin) Topical Parasiticide is available as a colorless to yellow, ready to use solution in single dose tubes for topical (dermal) treatment of dogs six weeks of age and older and cats eight weeks of age and older. The content of each tube is formulated to provide a minimum of 2.7 mg/lb (6 mg/kg) of body weight of selamectin. The chemical composition of selamectin is (5Z,25S)-25-cyclohexyl-4'-O-de(2,6-dideoxy-3-O-methyl-α-L-arabino-hexopyranosyl)-5-demethoxy-25-de(1-methylpropyl)-22,23-dihydro-5-hydroxyiminoavermectin A1a.

INDICATIONS:

Revolt is recommended for use in dogs six weeks of age or older and cats eight weeks of age and older for the following parasites and indications:

Dogs:
Revolt kills adult fleas and prevents flea eggs from hatching for one month and is indicated for the prevention and control of flea infestations (Ctenocephalides felis), prevention of heartworm disease caused by Dirofilaria immitis, and the treatment and control of ear mite (Otodectes cynotis) infestations. Revolt also is indicated for the treatment and control of sarcoptic mange (Sarcoptes scabiei) and for the control of tick infestations due to Dermacentor variabilis.

Cats:
Revolt kills adult fleas and prevents flea eggs from hatching for one month and is indicated for the prevention and control of flea infestations (Ctenocephalides felis), prevention of heartworm disease caused by Dirofilaria immitis, and the treatment and control of ear mite (Otodectes cynotis) infestations. Revolt is also indicated for the treatment and control of roundworm (Toxocara cati) and intestinal hookworm (Ancylostoma tubaeforme) infections in cats.

DOSAGE AND ADMINISTRATION:

The recommended minimum dose is 2.7 mg selamectin per pound (6 mg/kg) of body weight.

Administer the entire contents of a single dose tube (or two tubes used in combination for dogs weighing over 130 pounds) of Revolt topically in accordance with the following tables.

Cats (lb) | Package Color | mg per tube | Potency (mg/mL) | Administered volume (mL)
Up to 5 | Rose | 15 mg | 60 | 0.25
5.1-15 | Blue | 45 mg | 60 | 0.75
15.1-22 | Taupe | 60 mg | 60 | 1.0

For cats over 22 lbs use the appropriate combination of tubes.

Dogs (lb) | Package Color | mg per tube | Potency (mg/mL) | Administered volume (mL)
Up to 5 | Rose | 15 mg | 60 | 0.25
5.1-10 | Purple | 30 mg | 120 | 0.25
10.1-20 | Brown | 60 mg | 120 | 0.5
20.1-40 | Maroon | 120 mg | 120 | 1.0
40.1-85 | Teal | 240 mg | 120 | 2.0
85.1-130 | Plum | 360 mg | 120 | 3.0

For dogs over 130 lbs use the appropriate combination of tubes. Recommended for use in dogs 6 weeks of age and older and in cats 8 weeks of age and older.

A veterinarian or veterinary technician should demonstrate or instruct the pet owner regarding the appropriate technique for applying Revolt topically to dogs and cats prior to first use.

While holding the tube in an upright position, twist the cap to break the seal. The cap will remain on the tube. To administer the product, part the hair on the back of the animal at the base of the neck in front of the shoulder blades until the skin is visible. Place the tip of the tube on the skin and squeeze the tube 3 or 4 times to empty its entire contents directly onto the skin in one spot. Keeping the tube squeezed, drag it away from the liquid and lift to remove. Check the tube to ensure that it is empty.

Do not massage the product into the skin. Due to alcohol content, do not apply to broken skin. Avoid contact between the product and fingers. Do not apply when the haircoat is wet. Bathing or shampooing the dog 2 or more hours after treatment will not reduce the effectiveness of Revolt against fleas or heartworm. Bathing or shampooing the cat 2 hours after treatment will not reduce the effectiveness of Revolt against fleas. Bathing or shampooing the cat 24 hours after treatment will not reduce the effectiveness of Revolt against heartworm.

Stiff hair, clumping of hair, hair discoloration, or a slight powdery residue may be observed at the treatment site in some animals. These effects are temporary and do not affect the safety or effectiveness of the product. Discard empty tubes in your ordinary household refuse.

Flea Control in Dogs and Cats
For the prevention and control of flea infestations, Revolt should be administered at monthly intervals throughout the flea season, starting one month before fleas become active. In controlled laboratory studies >98% of fleas were killed within 36 hours. Results of clinical field studies using selamectin monthly demonstrated >90% control of flea infestations within 30 days of the first dose. Dogs and cats treated with selamectin, including those with pre-existing flea allergy dermatitis, showed improvement in clinical signs associated with fleas as a direct result of eliminating the fleas from the animals and their environment.

If the dog or cat is already infested with fleas when the first dose of Revolt is administered, adult fleas on the animal are killed and no viable fleas hatch from eggs after the first administration. However, an environmental infestation of fleas may persist for a short time after beginning treatment with Revolt because of the emergence of adult fleas from pupae.

Heartworm Prevention in Dogs and Cats
For the prevention of heartworm disease, Revolt must be administered on a monthly basis. Revolt may be administered year-round or at least within one month after the animal’s first exposure to mosquitoes and monthly thereafter until the end of the mosquito season. The final dose must be given within one month after the last exposure to mosquitoes. If a dose is missed and a monthly interval between dosing is exceeded then immediate administration of Revolt and resumption of monthly dosing will minimize the opportunity for the development of adult heartworms. When replacing another heartworm preventive product in a heartworm disease prevention program, the first dose of Revolt must be given within a month of the last dose of the former medication.

Selamectin, the active ingredient in Revolt, is a macrocyclic lactone compound. These compounds effectively prevent the development of adult heartworms when administered to dogs and cats within one month of exposure to infective (L3) Dirofilaria immitis larvae. Efficacy of macrocyclic lactones decreases below 100% in dogs, however, if first administered >2 months after exposure to infective larvae. Thus, in heartworm endemic regions, delaying initiation of heartworm prevention using Revolt beyond 2 months of first exposure to infective larvae (e.g., starting puppies and kittens at >8 weeks of age), or gaps of >2 months in the administration of Revolt during periods of heartworm transmission, increases the risk of the animal acquiring heartworms. Animals with unknown heartworm history that test negative for heartworms prior to the initiation of Revolt may be harboring pre-patent infections at the time Revolt was started. Testing such animals 3–4 months after initiation of Revolt would be necessary to confirm their negative heartworm status.

At the discretion of the veterinarian, cats ≥ 6 months of age may be tested to determine the presence of existing heartworm infections before beginning treatment with Revolt. Cats already infected with adult heartworms can be given Revolt monthly to prevent further infections.

Ear Mite Treatment in Dogs and Cats
For the treatment of ear mite (O. cynotis) infestations in dogs and cats, Revolt should be administered once as a single topical dose. A second monthly dose may be required in some dogs. Monthly use of Revolt will control any subsequent ear mite infestations. In the clinical field trials ears were not cleaned, and many animals still had debris in their ears after the second dose. Cleansing of the infested ears is recommended to remove the debris.

Sarcoptic Mange Treatment in Dogs
For the treatment of sarcoptic mange (S. scabiei) in dogs, Revolt should be administered once as a single topical dose. A second monthly dose may be required in some dogs. Monthly use of Revolt will control any subsequent sarcoptic mange mite infestations. Because of the difficulty in finding sarcoptic mange mites on skin scrapings, effectiveness assessments also were based on resolution of clinical signs. Resolution of the pruritus associated with the mite infestations was observed in approximately 50% of the dogs 30 days after the first treatment and in approximately 90% of the dogs 30 days after the second monthly treatment.

Tick Control in Dogs
For the control of tick (Dermacentor variabilis) infestations in dogs, Revolt should be administered on a monthly basis. In heavy tick infestations, complete efficacy may not be achieved after the first dose. In these cases, one additional dose may be administered two weeks after the previous dose, with monthly dosing continued thereafter.

Nematode Treatment in Cats
For the treatment and control of intestinal hookworm (A. tubaeforme) and roundworm (T. cati) infections, Revolt should be applied once as a single topical dose.

WARNINGS:

User Safety Warnings

Not for human use. Keep out of the reach of children. In humans, Revolt may be irritating to skin and eyes.

Reactions such as hives, itching and skin redness have been reported in humans. Individuals with known hypersensitivity to Revolt should use the product with caution or consult a health care professional. Revolt contains isopropyl alcohol and the preservative butylated hydroxytoluene (BHT). Wash hands after use and wash off any product in contact with the skin immediately with soap and water. If contact with eyes occurs, then flush eyes copiously with water; if wearing contact lenses, rinse eyes first then remove contact lenses and continue to rinse for 5-10 minutes and seek medical attention. In case of ingestion by a human, contact a physician immediately. The safety data sheet (SDS) provides more detailed occupational safety information. To obtain a SDS contact Aurora Pharmaceutical at 1-888-215-1256 or www.aurorapharmaceutical.com.

Flammable - Keep away from heat, sparks, open flames or other sources of ignition.

Animal Safety Warnings

Do not use in sick, debilitated or underweight animals (see TARGET ANIMAL SAFETY).

PRECAUTIONS:

Prior to administration of Revolt, dogs should be tested for existing heartworm infections. At the discretion of the veterinarian, infected dogs should be treated to remove adult heartworms. Revolt is not effective against adult D. immitis and, while the number of circulating microfilariae may decrease following treatment, Revolt is not effective for microfilariae clearance.

Hypersensitivity reactions have not been observed in dogs with patent heartworm infections administered selamectin (See TARGET ANIMAL SAFETY).

ADVERSE REACTIONS:

Pre-approval clinical trials:
Following treatment with selamectin, transient localized alopecia with or without inflammation at or near the site of application was observed in approximately 1% of 691 treated cats. Other signs observed (≤0.5% of 1743 treated cats and dogs) included vomiting, loose stool or diarrhea with or without blood, anorexia, lethargy, salivation, tachypnea, and muscle tremors.

Post-approval experience (2021):
The following adverse events are based on post-approval adverse drug experience reporting for selemectin. Not all adverse events are reported to FDA/CVM. It is not always possible to reliably estimate the adverse event frequency or establish a causal relationship to product exposure using this data.

The following adverse events reported for dogs are listed in decreasing order of reporting frequency: Lethargy, vomiting, diarrhea, anorexia, generalized pruritus, seizures, application site reactions (including alopecia, lesions, erythema, pruritis, and inflammation), tremors, ataxia, death, and dermatitis.

The following adverse events reported for cats are listed in decreasing order of reporting frequency: Application site reactions (including alopecia, lesions, erythema, pruritus, inflammation, vesicles, blisters, and excoriations), lethargy, anorexia, vomiting, death, generalized pruritus, diarrhea, ataxia, fever, generalized alopecia, tremors, hypersalivation, dermatitis, and seizures.

Contact Information:

To report suspected adverse drug events, for technical assistance or to obtain a copy of the SDS, contact Aurora Pharmaceutical at 1-888-215-1256 or www.aurorapharmaceutical.com. For additional information about adverse drug experience reporting for animal drugs, contact FDA at 1-888-FDA-VETS or online at www.fda.gov/reportanimalae

TARGET ANIMAL SAFETY:

Selamectin has been tested safe in over 100 different pure and mixed breeds of healthy dogs and over 15 different pure and mixed breeds of healthy cats, including pregnant and lactating females, breeding males and females, puppies six weeks of age and older, kittens eight weeks of age and older, and avermectin-sensitive collies. A kitten, estimated to be 5–6 weeks old (0.3 kg), died 8 1/2 hours after receiving a single treatment of selamectin at the recommended dosage. The kitten displayed clinical signs which included muscle spasms, salivation and neurological signs. The kitten was a stray with an unknown history and was malnourished and underweight (see WARNINGS).

DOGS: In safety studies, selamectin was administered at 1, 3, 5, and 10 times the recommended dose to six-week-old puppies, and no adverse reactions were observed. The safety of selamectin administered orally also was tested in case of accidental oral ingestion. Oral administration of selamectin at the recommended topical dose in 5- to 8-month-old beagles did not cause any adverse reactions. In a pre-clinical study selamectin was dosed orally to ivermectin-sensitive collies. Oral administration of 2.5, 10, and 15 mg/kg in this dose escalating study did not cause any adverse reactions; however, eight hours after receiving 5 mg/kg orally, one avermectin-sensitive collie became ataxic for several hours, but did not show any other adverse reactions after receiving subsequent doses of 10 and 15 mg/kg orally. In a topical safety study conducted with avermectin-sensitive collies at 1, 3 and 5 times the recommended dose of selamectin, salivation was observed in all treatment groups, including the vehicle control. Selamectin also was administered at 3 times the recommended dose to heartworm infected dogs, and no adverse effects were observed.

CATS: In safety studies, selamectin was applied at 1, 3, 5, and 10 times the recommended dose to six-week-old kittens. No adverse reactions were observed. The safety of selamectin administered orally also was tested in case of accidental oral ingestion. Oral administration of the recommended topical dose of selamectin to cats caused salivation and intermittent vomiting. Selamectin also was applied at 4 times the recommended dose to patent heartworm infected cats, and no adverse reactions were observed.

In well-controlled clinical studies, selamectin was used safely in animals receiving other frequently used veterinary products such as vaccines, anthelmintics, antiparasitics, antibiotics, steroids, collars, shampoos and dips.

STORAGE CONDITIONS:

Store below 30°C (86°F).

HOW SUPPLIED:

Available in eight separate dose strengths for dogs and cats of different weights (see DOSAGE). Revolt for puppies and kittens is available in cartons containing 3 single dose tubes. Revolt for cats and dogs is available in cartons containing 3 or 6 single dose tubes.

Approved by FDA under ANADA # 200-673

Revolt® (selamectin)

Manufactured By:

Aurora Pharmaceutical, Inc.

NORTHFIELD, MN 55057

www.aurorapharmaceutical.com

Aurora Pharmaceutical®

Manufactured In U.S.A

Client Information About Revolt® (selamectin) Revolt (pronounced “Re-volt”) Generic name: selamectin (“sel-a-mec-tin”)

This summary contains important information about Revolt. You should read this information before you start using Revolt on your dog or cat and review it each time your prescription is refilled. This sheet is provided only as a summary and does not take the place of instructions from your veterinarian. Talk to your veterinarian if you do not understand any of this information or if you want to know more about Revolt.

What is Revolt?
Revolt is a topical parasiticide that is applied to the skin of dogs six weeks of age and older and cats eight weeks of age and older to kill adult fleas and prevent flea eggs from hatching, prevent heartworm disease and protect your pet against other parasites (see below).

Why has my veterinarian prescribed Revolt?
Revolt has been prescribed by your veterinarian to treat, prevent and/or control the following parasites in your dog or cat:

Dog Parasites:

• Control and prevention of flea infestation (Ctenocephalides felis)
• Prevention of heartworm disease (Dirofilaria immitis)
• Treatment and control of ear mite infestation (Otodectes cynotis)
• Treatment and control of sarcoptic mange (Sarcoptes scabiei)
• Control of the American Dog Tick (Dermacentor variabilis)

Cat Parasites:

• Control and prevention of flea infestation (Ctenocephalides felis)
• Prevention of heartworm disease (Dirofilaria immitis)
• Treatment and control of ear mite infestation (Otodectes cynotis)
• Treatment and control of intestinal worms - Roundworm (Toxocara cati), Hookworm (Ancylostoma tubaeforme)

What should I discuss with my veterinarian before Revolt is prescribed?
Your veterinarian is best suited to discuss and recommend appropriate medications for your dog or cat. It is important to discuss your pet’s health history with your veterinarian so he/she can decide if Revolt is right for your animal.

Revolt should not be used in sick, debilitated or underweight animals.

Dogs should be tested for heartworm disease prior to giving Revolt. If your dog tests positive for adult heartworms, your veterinarian can recommend appropriate treatment. Dogs infected with adult heartworms can safely be given Revolt.

If your cat is older than six months of age, your veterinarian may decide to test him/her for heartworm disease before prescribing Revolt. Cats infected with adult heartworms can be given Revolt to prevent further infections.

What dose of Revolt do I use on my dog or cat?
Your veterinarian will recommend the appropriate dose for your dog or cat based on your animal’s body weight. You should not administer Revolt to dogs younger than 6 weeks of age or cats younger than 8 weeks of age. Revolt is available in eight separate dose strengths for dogs and cats of different weights.

What should I do if I do not give Revolt on time or miss a dose?
If you forget to apply a monthly dose of Revolt, immediately apply Revolt, resume monthly applications, and notify your veterinarian.

What if I administer more than the prescribed amount of Revolt to my dog or cat?
Contact your veterinarian if you administer more than the prescribed amount of Revolt.

How should Revolt be applied?

1. Remove the Revolt tube from its protective package.

2. While holding the tube in an upright position, twist the cap to break the seal. The cap will remain on the tube.

3. Part the hair on the back of the animal at the base of the neck, in front of the shoulder blades, until the skin is visible.

4. Apply the tip of the Revolt tube directly to the skin. Squeeze the tube firmly 3 to 4 times in one spot until empty. Keep the tube compressed on the final squeeze to avoid drawing liquid back into tube. Avoid contact between Revolt and your fingers.

5. While keeping tube squeezed, drag it away from liquid and lift up to remove.

6. Ensure tube is empty.

Do not massage Revolt into the skin.

Do not apply when the haircoat is wet.

Do not apply to broken skin – Revolt contains alcohol.

Stiff hair, clumping of hair, hair discoloration, or a slight powdery residue may be observed at the site in some animals. These effects are usually temporary and do not affect the safety or effectiveness of the product.

Can I give my pet a bath after applying Revolt?
Yes. Bathing or shampooing the dog 2 or more hours after treatment will not reduce the effectiveness of Revolt against fleas or heartworm. Bathing or shampooing the cat 2 hours after treatment will not reduce the effectiveness of Revolt against fleas. Bathing or shampooing the cat 24 hours after treatment will not reduce the effectiveness of Revolt against heartworm.

When can I play with my pet following treatment with Revolt?

You should avoid contact with application site when wet. You may hold or play with your pet any time after the area on which Revolt was applied is dry.

I see fleas on my dog or cat. Is Revolt working?
Revolt kills adult fleas and prevents flea eggs from hatching. You may occasionally see a few fleas on dogs or cats treated with Revolt but more than 98% of adult fleas are killed within 36 hours.

Immature stages of the flea called pupae may be present in your pets’ environment (yard, flooring, carpet, bedding, etc.). These pupae are not killed by parasiticides (including Revolt) and as such may emerge as adult fleas. These adult fleas may hop onto your pet at any time. They must be exposed to Revolt on your dog or cat before being killed. It can take from 3 to 5 weeks (or longer depending on environmental conditions) for most fleas to complete their 4-stage life cycle (egg, larvae, pupae, and adult) and reach the adult stage before being seen on your pet. Due to the presence of immature flea stages in infested environments it can take up to 2 to 3 monthly applications for Revolt to maximally control the infestation of fleas in the environment. Once the flea population is controlled you will be less likely to see fleas.

I see ticks on my dog. Is Revolt working?
Revolt controls tick infestations only due to the American Dog Tick (Dermacentor variabilis), a tick commonly found on dogs. There are other common species of ticks that are not killed or controlled by Revolt. Your veterinarian can recommend appropriate products to control or kill ticks common to your area. For the control of the American Dog Tick, Revolt should be applied once a month; however, your veterinarian may recommend a second administration applied 14 days after the first dose if your dog has a heavy tick infestation and/or recommend additional tick control methods. It may take up to 5 days to kill the majority of ticks on your dog.

What are the possible side effects of Revolt?
Like all medicines, Revolt has some side effects. The most common is hair loss at the site of application with or without inflammation (redness, flaking) in cats. Other side effects reported in cats and dogs include vomiting, diarrhea with or without blood, anorexia (decreased appetite), lethargy (sluggishness), salivation, rapid breathing, pruritus (itching), urticaria (welts, hives), erythema (skin redness), ataxia (incoordination), fever and rare instances of death. There have also been rare reports of seizures in dogs.

If you have additional questions about possible side effects, talk to your veterinarian.

Can Revolt be given with other medicines?
In well-controlled clinical studies, selamectin was used safely in dogs and cats receiving other veterinary products such as vaccines, anthelmintics, antiparasitics, antibiotics, steroids, collars, shampoos and dips.

Tell your veterinarian about all medicines you have given your dog or cat in the past, and any medicines that you are planning to use with Revolt. This should include other medicines that you can get without a prescription. Your veterinarian may want to check that all of your dog’s or cat’s medicines can be given together.

How should Revolt be stored?
Revolt is flammable – Keep away from heat, sparks, open flames or other sources of ignition. Store below 30°C (86°F). After application, empty tubes can be placed in your normal household refuse for disposal.

What else should I know about Revolt?
Revolt is not for use in humans. Revolt should be kept out of reach of children. In humans, Revolt may be irritating to skin and eyes. Reactions such as hives, itching and skin redness have been reported in humans in rare instances. Individuals with known hypersensitivity to Revolt should use the product with caution or consult a health care professional. Revolt contains isopropyl alcohol and the preservative butylated hydroxytoluene (BHT). Wash hands after use and wash off any product in contact with the skin immediately with soap and water. In case of human ingestion contact a doctor immediately.

Approved by FDA under ANADA #200-673

Revised: 08/2023

PRINCIPAL DISPLAY PANEL - 15 MG TUBE CARTON

For puppies ≤ 5 lbs in weight and at least 6 weeks of age and kittens ≤ 5 lbs in weight and at least 8 weeks of age

Three single-dose tubes each containing 0.25 mL (15 mg) of selamectin

NDC 51072-097-01

0.25 mL

Revolt® (selamectin)

Administer once a month to prevent heartworm disease and prevent and control flea infestations

aurora pharmaceutical®

Caution: U.S. Federal law restricts this drug to use by or on the order of a licensed veterinarian.

For use in animals only. Keep out of reach of children.

Approved by FDA under ANADA # 200-673

3 Doses

IN 40-1577

Rev. 08/2023

REORDER NO: 17003

PRINCIPAL DISPLAY PANEL - 30 MG TUBE CARTON

For dogs 5.1-10 lbs in weight and at least 6 weeks of age

Three single-dose tubes each containing 0.25 mL (30 mg) of selamectin

NDC 51072-098-06

0.25 mL

Revolt® (selamectin)

Administer once a month to prevent heartworm disease and prevent and control flea infestations

aurora pharmaceutical®

Caution: U.S. Federal law restricts this drug to use by or on the order of a licensed veterinarian.

For use in animals only. Keep out of reach of children.

Approved by FDA under ANADA # 200-673

3 Doses

IN 40-1597

Rev. 02/2021

REORDER NO: 16009

PRINCIPAL DISPLAY PANEL - 45 MG TUBE CARTON

Topical solution for cats 5.1-15 lbs in weight and at least 8 weeks of age

Three single-dose tubes each containing 0.75 mL (45 mg) of selamectin

NDC 51072-097-04

0.75 mL

Revolt® (selamectin)

Administer topically once a month for protection against fleas and heartworm disease and treatment and control of hookworms, roundworms, and ear mites

aurora pharmaceutical®

Caution: U.S. Federal law restricts this drug to use by or on the order of a licensed veterinarian.

For use in animals only. Keep out of reach of children.

Approved by FDA under ANADA # 200-673

3 Doses

IN 40-1595

Rev. 08/2023

REORDER NO: 17004

PRINCIPAL DISPLAY PANEL - 60 MG [1 ML] TUBE CARTON

For cats 15.1-22 lbs in weight and at least 8 weeks of age

Three single-dose tubes each containing 1.0 mL (60 mg) of selamectin

NDC 51072-097-05

1.0 mL

Revolt® (selamectin)

Administer once a month for protection against fleas and heartworm disease and treatment and control of hookworms, roundworms, and ear mites

aurora pharmaceutical®

Caution: U.S. Federal law restricts this drug to use by or on the order of a licensed veterinarian.

For use in animals only. Keep out of reach of children.

Approved by FDA under ANADA # 200-673

3 Doses

IN 40-1596

Rev. 02/2021

REORDER NO: 17006

PRINCIPAL DISPLAY PANEL - 60 MG [0.5 ML] TUBE CARTON

For dogs 10.1-20 lbs in weight and at least 6 weeks of age

Three single-dose tubes each containing 0.5 mL (60 mg) of selamectin

NDC 51072-098-07

0.5 mL

Revolt® (selamectin)

Administer once a month to prevent heartworm disease and prevent and control flea infestations

aurora pharmaceutical®

Caution: U.S. Federal law restricts this drug to use by or on the order of a licensed veterinarian.

For use in animals only. Keep out of reach of children.

Approved by FDA under ANADA # 200-673

3 Doses

IN 40-1598

Rev. 02/2021

REORDER NO: 16011

PRINCIPAL DISPLAY PANEL - 120 MG TUBE CARTON

For dogs 20.1-40 lbs in weight and at least 6 weeks of age

Three single-dose tubes each containing 1.0 mL (120 mg) of selamectin

NDC 51072-098-08

1.0 mL

Revolt® (selamectin)

Administer once a month to prevent heartworm disease and prevent and control flea infestations

aurora pharmaceutical®

Caution: U.S. Federal law restricts this drug to use by or on the order of a licensed veterinarian.

For use in animals only. Keep out of reach of children.

Approved by FDA under ANADA # 200-673

3 Doses

IN 40-1599

Rev. 02/2021

REORDER NO: 16013

PRINCIPAL DISPLAY PANEL - 240 MG TUBE CARTON

For dogs 40.1-85 lbs in weight and at least 6 weeks of age

Three single-dose tubes each containing 2.0 mL (240 mg) of selamectin

NDC 51072-098-09

2.0 mL

Revolt® (selamectin)

Administer once a month to prevent heartworm disease and prevent and control flea infestations

aurora pharmaceutical®

Caution: U.S. Federal law restricts this drug to use by or on the order of a licensed veterinarian.

For use in animals only. Keep out of reach of children.

Approved by FDA under ANADA # 200-673

3 Doses

IN 40-1600

Rev. 02/2021

REORDER NO: 16015

PRINCIPAL DISPLAY PANEL - 360 MG TUBE CARTON

For dogs 85.1-130 lbs in weight and at least 6 weeks of age

Three single-dose tubes each containing 3.0 mL (360 mg) of selamectin

NDC 51072-098-10

3.0 mL

Revolt® (selamectin)

Administer once a month to prevent heartworm disease and prevent and control flea infestations

aurora pharmaceutical®

Caution: U.S. Federal law restricts this drug to use by or on the order of a licensed veterinarian.

For use in animals only. Keep out of reach of children.

Approved by FDA under ANADA # 200-673

3 Doses

IN 40-1601

Rev. 02/2021

REORDER NO: 16017